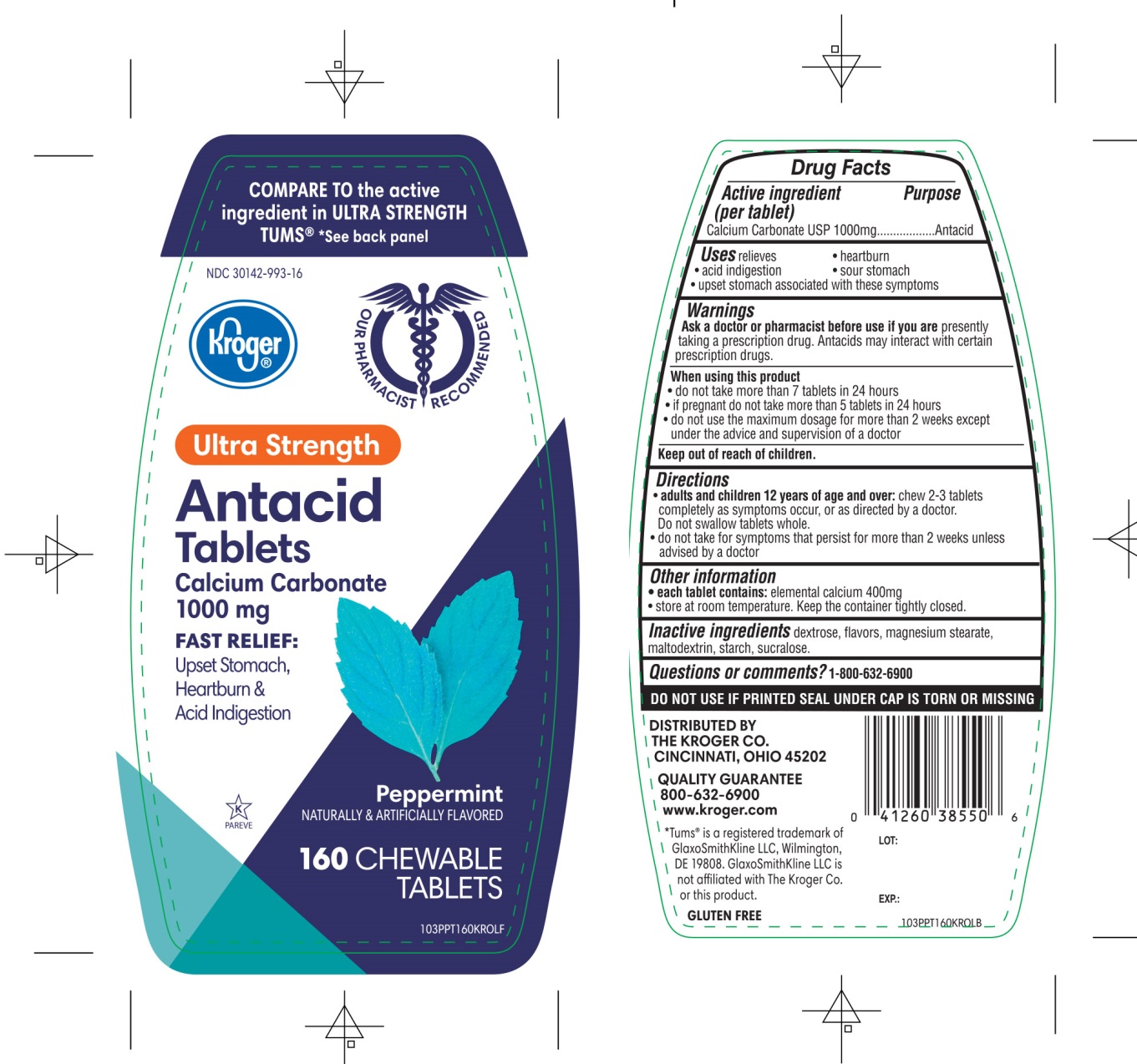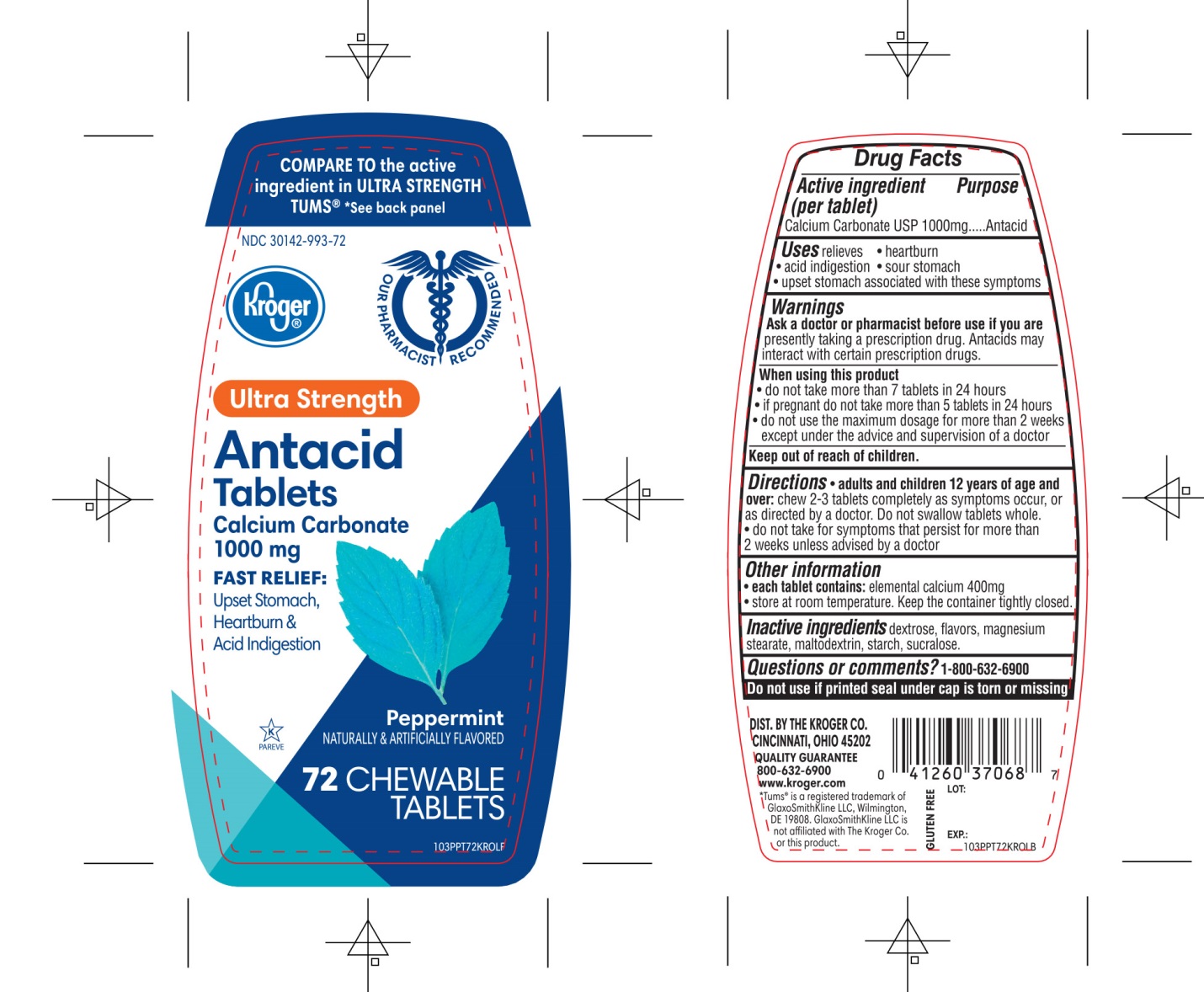 DRUG LABEL: Ultra Strength Antacid
NDC: 30142-993 | Form: TABLET, CHEWABLE
Manufacturer: THE KROGER CO.,
Category: otc | Type: HUMAN OTC DRUG LABEL
Date: 20250801

ACTIVE INGREDIENTS: CALCIUM CARBONATE 1000 mg/1 1
INACTIVE INGREDIENTS: DEXTROSE, UNSPECIFIED FORM; MAGNESIUM STEARATE; MALTODEXTRIN; STARCH, CORN; SUCRALOSE

Kroger Ultra Strength Antacid Tablets Calcium Carbonate 1000mg Peppermint Flavor

Active ingredient (per tablet)

Calcium Carbonate USP 1000mg

Purpose

Antacid

Uses

relieves

- heartburn
- acid indigestion
- sour stomach
- upset stomach associated with these symptoms

Warnings

Ask a doctor or pharmacist before use if you arepresently taking a prescription drug. Antacids may interact with certain prescription drugs.

When using this product

- do not take more than 7 tablets in 24 hours
- if pregnant do not take more than 5 tablets in 24 hours
- do not use the maximum dosage for more than 2 weeks except under the advice and supervision of a doctor.

Directions

- adults and children 12 years of age and over:chew 2-3 tablets as symptoms occur, or as directed by a doctor
- do not take for symptoms that persist for more than 2 weeks unless advised by a doctor

Other information

- each tablet contains : elemental calcium 400mg
- store at room temperature. Keep the container tightly closed.

Inactive ingredients

dextrose, flavors, magnesium stearate, maltodextrin, starch, sucralose.

Questions?

1-800-632-6900

Safety sealed: Do not use if printed seal under cap is torn or missing

Package/Label Principal Display Panel

Kroger®

COMPARE TO the active ingredient of Tums® Ultra Strength

- *See back Panel
- FAST RELIEF OF UPSET STOMACH, HEARTBURN, AND ACID INDIGESTION

ULTRA STRENGTH

Antacid

Tablets

Calcium Carbonate USP 1,000 mg

Peppermint Flavor

NATURALLY AND ARTIFICIALLY FLAVORED

DISTRIBUTED BY THE KROGER CO., CINCINNATI, OHIO 45202

QUALITY GUARANTEE

1800-632-6900

www.Kroger.com

GLUTEN FREE

*TUMS®IS A REGISTERED TRADEMARK OF GLAXOSMITHKLINE LLC, WILMINGTON, DE 19808, GLAXOSMITHKLINE LLC IS NOT AFFILIATED WITH THE KROGER CO, OR THIS PRODUCT

Package Label 160 Chewable Tablets